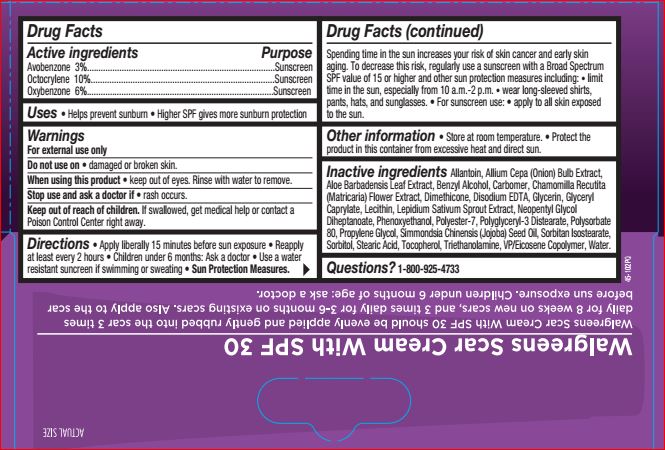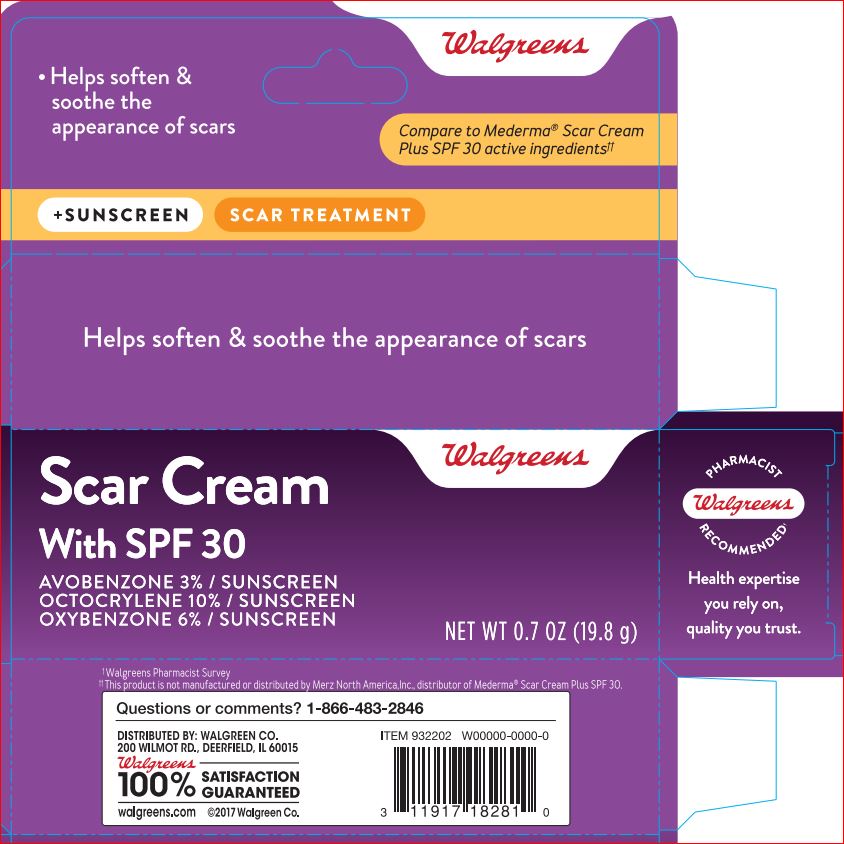 DRUG LABEL: Scar with SPF 30
NDC: 0363-1116 | Form: CREAM
Manufacturer: Walgreens
Category: otc | Type: HUMAN OTC DRUG LABEL
Date: 20180629

ACTIVE INGREDIENTS: Avobenzone 3 g/100 g; Octocrylene 10 g/100 g; Oxybenzone 6 g/100 g
INACTIVE INGREDIENTS: Water; ONION; Sorbitan Isostearate; Sorbitol; Polyester-7; VINYLPYRROLIDONE/EICOSENE COPOLYMER; GLYCERYL MONOCAPRYLATE; ALOE VERA LEAF; CHAMOMILE; JOJOBA OIL; GARDEN CRESS SPROUT; Allantoin; Tocopherol; Stearic Acid; Polysorbate 80; Dimethicone; Propylene Glycol; EDETATE DISODIUM; Glycerin; Neopentyl Glycol Diheptanoate; Polyglyceryl-3 Distearate; Benzyl Alcohol; TROLAMINE; Phenoxyethanol

Drug Facts

Active ingredients Purpose
Avobenzone 3% ......................................... Sunscreen
Octocrylene, 10% ....................................... Sunscreen
Oxybenzone 6% ......................................... Sunscreen

Uses
• Helps prevent sunburn • Higher SPF gives more sunburn protection

Warnings For External use only

Warnings
For external use only
Do not use on • damaged or broken skin.
When using this product • keep out of eyes. Rinse with water to remove.
Stop use and ask a doctor if • rash occurs.
Keep out of reach of children. If swallowed, get medical help or contact a
Poison Control Center right away

Keep out of reach of children. If swallowed, get medical help or contact a Poison Control Center right
away.

DOSAGE AND ADMINISTRATION

Directions • Apply liberally 15 minutes before sun exposure • Reapply
at least every 2 hours • Children under 6 months: Ask a doctor • Use a water
resistant suncreen if swimming or sweating • Sun Protection Measures.

Spending time in the sun increases your risk of skin cancer and early skin
aging. To decrease this risk, regularly use a sunscreen with a Broad Spectrum
SPF value of 15 or higher and other sun protection measures including: • limit
time in the sun, especially from 10 a.m.-2 p.m. • wear long-sleeved shirts,
pants, hats, and sunglasses. • For sunscreen use: • apply to all skin exposed
to the sun.

Other information • Store at room temperature. • Protect the
product in this container from excessive heat and direct sun.

Inactive ingredients Allantoin, Allium Cepa (Onion) Bulb Extract,
Aloe Barbadensis Leaf Extract, Benzyl Alcohol, Carbomer, Chamomilla Recutita
(Matricaria) Flower Extract, Dimethicone, Disodium EDTA, Glycerin, Glyceryl
Caprylate, Lecithin, Lepidium Sativum Sprout Extract, Neopentyl Glycol
Diheptanoate, Phenoxyethanol, Polyester-7, Polyglyceryl-3 Distearate, Polysorbate
80, Propylene Glycol, Simmondsia Chinensis (Jojoba) Seed Oil, Sorbitan Isostearate,
Sorbitol, Stearic Acid, Tocopherol, Triethanolamine, VP/Eicosene Copolymer, Water.